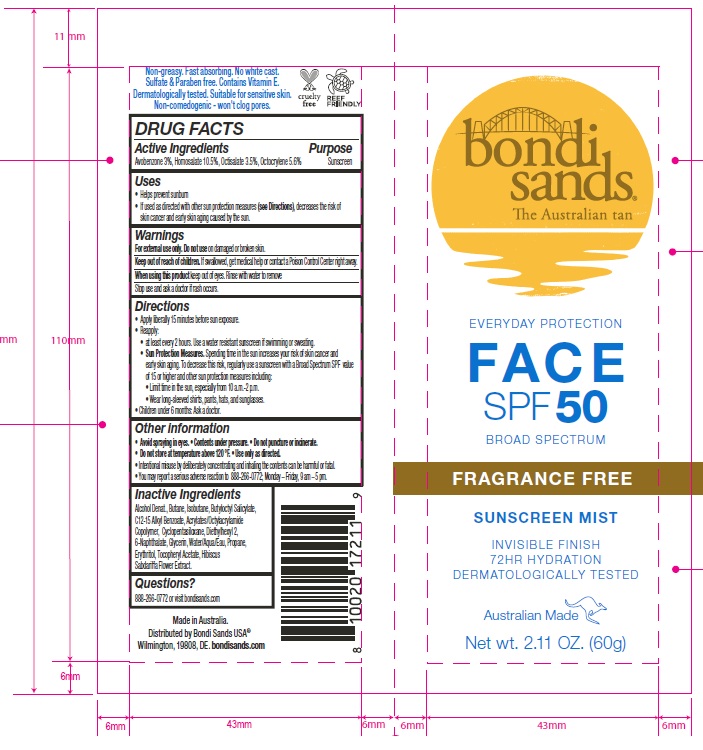 DRUG LABEL: Bondi Sands Fragrance Free Face SPF 50 Sunscreen Mist
NDC: 79950-022 | Form: AEROSOL, SPRAY
Manufacturer: BONDI SANDS (USA) INC.
Category: otc | Type: HUMAN OTC DRUG LABEL
Date: 20250210

ACTIVE INGREDIENTS: OCTOCRYLENE 56 mg/1 g; AVOBENZONE 30 mg/1 g; HOMOSALATE 105 mg/1 g; OCTISALATE 35 mg/1 g
INACTIVE INGREDIENTS: BUTYLOCTYL SALICYLATE; C12-15 ALKYL BENZOATE; GLYCERIN; PROPANE; ISOBUTANE; ACRYLATES/OCTYLACRYLAMIDE COPOLYMER (75000 MW); ALCOHOL; BUTANE; CYCLOPENTASILOXANE; ERYTHRITOL; .ALPHA.-TOCOPHEROL ACETATE; DIETHYLHEXYL 2,6-NAPHTHALATE; WATER

Bondi Sands Fragrance Free Face SPF 50 Sunscreen Mist

Active Ingredients

Avobenzone 3%

Homosalate 10.5%

Octisalate 3.5%

Octocrylene 5.6%

Purpose

Sunscreen

Uses

- Helps prevent sunburn.
- If used as directed with other sun protection measures (see Directions), decreases the risk of skin cancer and early skin aging caused by the sun.

Warnings

For external use only.

Do not use

on damaged or broken skin.

Keep out of reach of children.

If swallowed, get medical help or contact a Poison Control Center right away.

When using this product

keep out of eyes. Rinse with water to remove.

Stop use and ask a doctor

if rash occurs.

Directions

- Apply liberally 15 minutes before sun exposure.
- Reapply:
- at least every 2 hours. Use a water resistant sunscreen if swimming or sweating.
- Sun Protection Measures: Spending time in the sun increases your risk of skin cancer and early skin aging. To decrease this risk, regularly use a sunscreen with a Broad Spectrum SPF value of 15 or higher and other sun protection measures including:
- Limit time in the sun, especially from 10 a.m. - 2 p.m.
- Wear long-sleeved shirts, pants, hats, and sunglasses.
- Children under 6 months: Ask a doctor.

Other Information

- Avoid spraying in eyes.
- Contents under pressure.
- Do not puncture or incinerate.
- Do not store at temperature above 120F.
- Use only as directed.
- Intentional misuse by deliberately concentrating and inhaling can be harmful or fatal..
- You may report a serious adverse reaction to 888-266-0772; Monday-Friday, 9 am - 5 pm.

Inactive Ingredients

Alcohol Denat., Butane, Isobutane, Butyloctyl Salicylate, C12-15 Alkyl Benzoate, Acrylates/Octylacrylamide Copolymer, Cyclopentasiloxane, Diethylhexyl 2,6-Naphthalate, Glycerin, Water/Aqua/Eau, Propane, Erythritol, Tocopheryl Acetate, Hibiscus Sabdariffa Fruit Extract

Questions?

888-266-0772 or visit bondisands.com